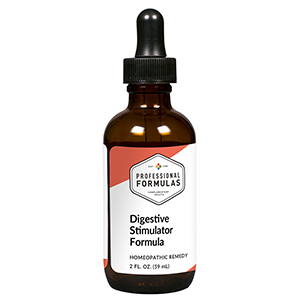 DRUG LABEL: Digestive Stimulator Formula
NDC: 63083-2069 | Form: LIQUID
Manufacturer: Professional Complementary Health Formulas
Category: homeopathic | Type: HUMAN OTC DRUG LABEL
Date: 20190815

ACTIVE INGREDIENTS: ASTRAGALUS PROPINQUUS ROOT 6 [hp_X]/59 mL; ASIAN GINSENG 3 [hp_X]/59 mL; GLYCYRRHIZA GLABRA 3 [hp_X]/59 mL; BARLEY 3 [hp_X]/59 mL; CODONOPSIS PILOSULA ROOT 3 [hp_X]/59 mL; ATRACTYLODES MACROCEPHALA ROOT 3 [hp_X]/59 mL; CHAENOMELES JAPONICA SEED 3 [hp_X]/59 mL
INACTIVE INGREDIENTS: ALCOHOL; WATER

C69

ACTIVE INGREDIENTS

Huang-Chi 6X, 12X, 30X
and all the following at 3X, 6X, 12X, 30X:
Jen-Shen
Kan-Tsao
Mai-Ya
Tang-Shen
Tsang-Chu
Yuan-Chih

QUESTIONS

Professional Formulas

PO Box 2034 Lake Oswego, OR 97035

INDICATIONS

For the temporary relief of indigestion, nausea, or vomiting.*

PURPOSE

*Claims based on traditional homeopathic practice, not accepted medical evidence. Not FDA evaluated.

WARNINGS

In case of overdose, get medical help or contact a poison control center right away.

Keep out of the reach of children.

PREGNANCY OR BREAST FEEDING

If pregnant or breastfeeding, ask a healthcare professional before use.

DIRECTIONS

Place drops under tongue 30 minutes before/after meals. Adults and children 12 years and over: Take 10 drops up to 3 times per day. Consult a physician for use in children under 12 years of age.

OTHER INFORMATION

Tamper resistant. If seal is broken, do not use. After opening, close container tightly and store at room temperature away from heat.

INACTIVE INGREDIENTS

20% ethanol, purified water.

LABEL

Est 1985

Professional Formulas

Complementary Health

Digestive Stimulator Formula

Homeopathic Remedy

2 FL. OZ. (59 mL)